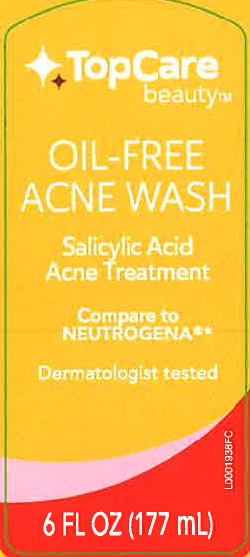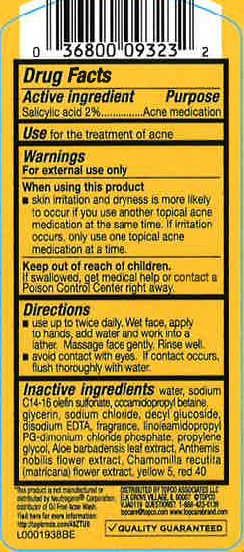 DRUG LABEL: Oil Free Acne Wash
NDC: 36800-947 | Form: LOTION
Manufacturer: Topco Associates LLC
Category: otc | Type: HUMAN OTC DRUG LABEL
Date: 20260213

ACTIVE INGREDIENTS: SALICYLIC ACID 20.6 mg/1 mL
INACTIVE INGREDIENTS: WATER; SODIUM C14-16 OLEFIN SULFONATE; COCAMIDOPROPYL BETAINE; GLYCERIN; SODIUM CHLORIDE; DECYL GLUCOSIDE; EDETATE DISODIUM ANHYDROUS; LINOLEAMIDOPROPYL PG-DIMONIUM CHLORIDE PHOSPHATE; PROPYLENE GLYCOL; ALOE VERA LEAF; CHAMAEMELUM NOBILE FLOWER; CHAMOMILE; FD&C YELLOW NO. 5; FD&C RED NO. 40

Top Care 947.003/947AC, AD
Oil Free Acne Wash

active ingredient

Salicylic Acid 2%

Purpose

Acne medication

Use

for the treatment of acne

Warnings

For external use only

When using this product

- skin irritation and dryness is more likely to occur if you use another topical acne medication at the same time. If irritation occurs, only use one topical acne medication at a time

Keep out of reach of children.

If swallowed, get medical help or contact a Poison Control Center right away.

Directions

- use up to twice a daily. Wet face, apply to hands, add water and work into lather. Massage face gently. Rinse well.
- avoid contact with eyes. If contact occurs, flush thoroughly with water.

Inactive ingredients

water, sodium C14-16 olefin sulfonate, cocamidopropyl betaine, glycerin, sodium chloride, decyl glucoside, disodium EDTA, fragrance, linoleamidopropyl PG-dimonium chloride phosphate, propylene glycol, Aloe barbadensis leaf extract, Anthemis nobilis flower extract, Chamomilla recutita (matricaria) flower extract, yellow 5, red 40

disclaimer

*This product is not manufactured or distributed by Neutrogena Corporation, distributor of Neutrogena®Oil Free Acne Wash.

Adverse Reactions Section

DISTRIBUTED BY TOPCO ASSOCIATES LLC

ELK GROVE VILLAGE, IL 60007

1-888-423-0139 TOPCO VIJ117

topcare@topco.com www.topcarebrand. com.

QUALITY GUARANTEED

principal display panel

Top Care

beauty™

OIL-FREE

ACNE WASH

Salicylic Acid

Acne treatment

Compare to NEUTROGENA®*

Dermatologist tested

6 FL OZ (177 mL)